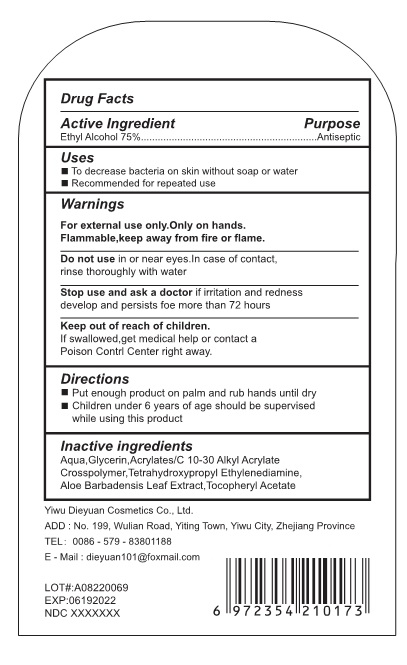 DRUG LABEL: Instant Hand Sanitizer
NDC: 75612-100 | Form: GEL
Manufacturer: Yiwu Dieyuan Cosmetics Co., Ltd.
Category: otc | Type: HUMAN OTC DRUG LABEL
Date: 20200623

ACTIVE INGREDIENTS: ALCOHOL 45 mL/60 mL
INACTIVE INGREDIENTS: .ALPHA.-TOCOPHEROL ACETATE; CARBOMER INTERPOLYMER TYPE A (ALLYL SUCROSE CROSSLINKED); GLYCERIN; EDETOL; WATER; ALOE VERA LEAF

75612-100

Active Ingredient(s)

Alcohol 75% v/v. Purpose: Antiseptic

Purpose

Antiseptic, Hand Sanitizer

Use

Hand Sanitizer to help reduce bacteria that potentially can cause disease. For use when soap and water are not available.

Warnings

1. This product is for external use, no taken orally, avoid contact with eyes, and keep away from reach of children.

2. Flammable, please keep away from the fire source; do not close to the fire source before no volatilized completely when use.

3. If there is skin irritation, please stop using. If further irritation, please consult a doctor and keep it below.

4. Use with caution for alcohol allergy.

Do not use

- in children less than 2 months of age
- on open skin wounds

When using this product keep out of eyes, ears, and mouth. In case of contact with eyes, rinse eyes thoroughly with water.
Stop use and ask a doctor if irritation or rash occurs. These may be signs of a serious condition.
Keep out of reach of children. If swallowed, get medical help or contact a Poison Control Center right away.

Stop use and ask a doctor if irritation or rash occurs. These may be signs of a serious condition.

Keep out of reach of children. If swallowed, get medical help or contact a Poison Control Center right away.

Directions

- Place enough product on hands to cover all surfaces. Rub hands together until dry.
- Supervise children under 6 years of age when using this product to avoid swallowing.

Other information

- Store between 15-30C (59-86F)
- Avoid freezing and excessive heat above 40C (104F)

Inactive ingredients

Aqua, glycerin, acrylates/C10-30 aklykl acrylate crosspolymer, tetrahydroxypropyl ethylenediamine, aloe barbadensis leaf extract, tocopheryl acetate

Package Label - Principal Display Panel

60 mL NDC: 75612-100-01